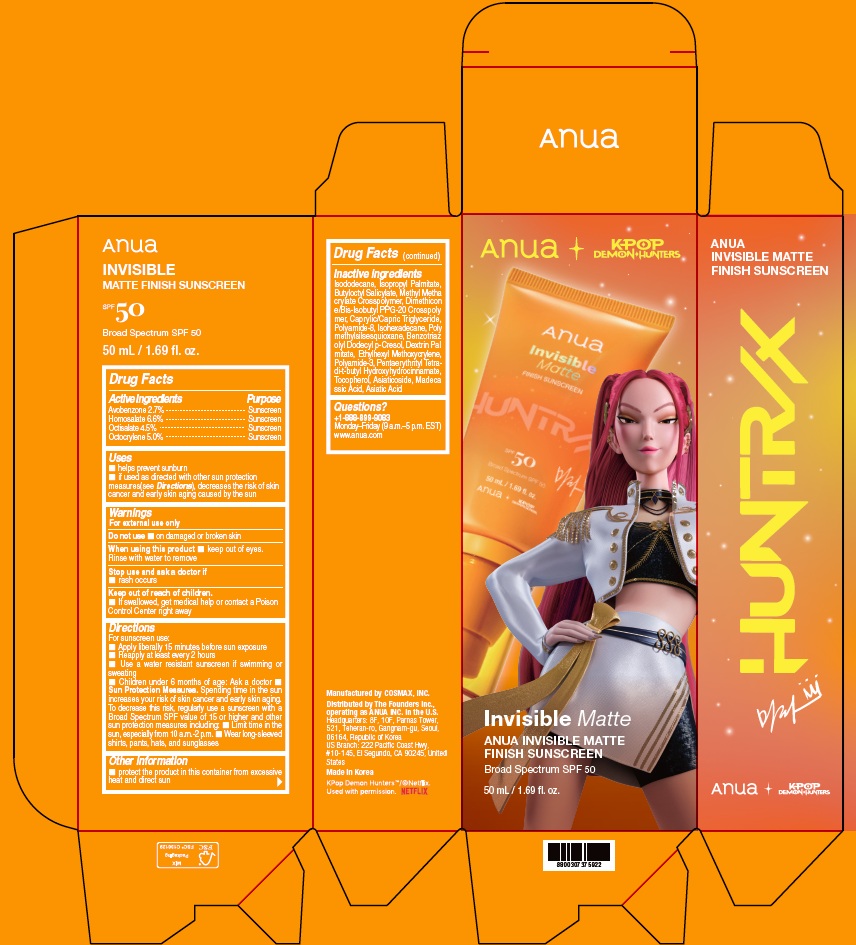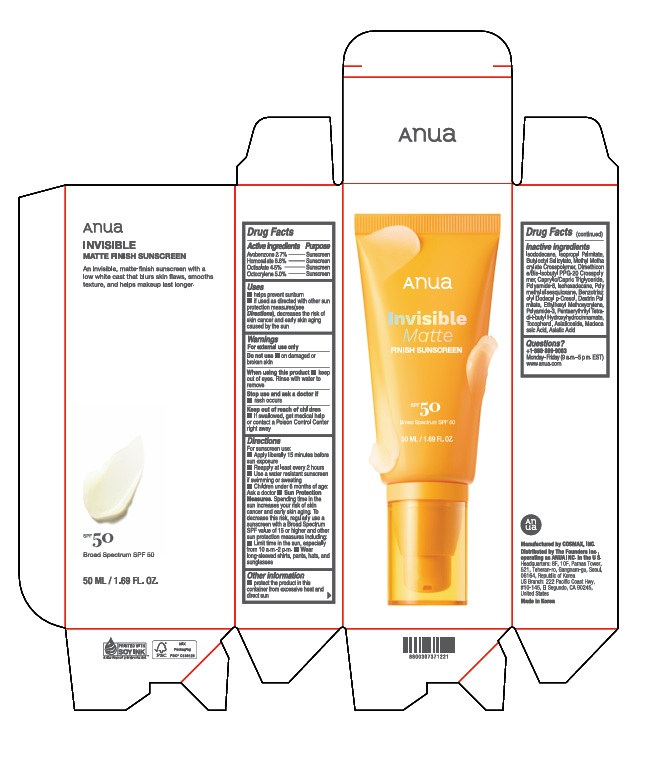 DRUG LABEL: ANUA INVISIBLE MATTE FINISH SUNSCREEN
NDC: 84610-400 | Form: CREAM
Manufacturer: The Founders Inc.
Category: otc | Type: HUMAN OTC DRUG LABEL
Date: 20260119

ACTIVE INGREDIENTS: HOMOSALATE 66 mg/1 mL; OCTISALATE 45 mg/1 mL; AVOBENZONE 27 mg/1 mL; OCTOCRYLENE 50 mg/1 mL
INACTIVE INGREDIENTS: CAPRYLIC/CAPRIC TRIGLYCERIDE; ISOHEXADECANE; ASIATICOSIDE; DIMETHICONE/BIS-ISOBUTYL PPG-20 CROSSPOLYMER; ISODODECANE; ASIATIC ACID; MADECASSIC ACID; ISOPROPYL PALMITATE; PENTAERYTHRITYL TETRA-DI-T-BUTYL HYDROXYHYDROCINNAMATE; TOCOPHEROL; BUTYLOCTYL SALICYLATE; ETHYLHEXYL METHOXYCRYLENE; BENZOTRIAZOLYL DODECYL P-CRESOL; POLYMETHYLSILSESQUIOXANE (4.5 MICRONS)

ANUA INVISIBLE MATTE FINISH SUNSCREEN

Drug Facts

Active Ingredients

Avobenzone 2.7%

Homosalate 6.6%

Octisalate 4.5%

Octocrylene 5.0%

Purpose

Sunscreen

Uses

- helps prevent sunburn
- if used as directed with other sun protection measures(see Diresctions), decreases the risk of skin cancer and early skin aging caused by the sun

Warnings

For external use only

Do not use

- on damaged or broken skin

When using this product

- keep out of eyes. Rinse with water to remove

Stop use and ask a doctor if

- rash occurs

Keep out of reach of children.

- If swallowed, get medical help or contact a Poison Control Center right away

Directions

For sunscreen use:

- Apply liberally 15 minutes before sun exposure
- Reapply at least every 2 hours
- Use a water resistant sunscreen if swimming or sweating
- Children under 6 months of age: Ask a doctor
- Sun Protection Measures. Spending time in the sun increases your risk of skin cancer and early skin aging. To decrease this risk, regularly use a sunscreen with a Broad Spectrum SPF value of 15 or higher and other sun protection measures including:
- Limit time in the sun, especially from 10 a.m.-2 p.m.
- Wear long-sleeved shirts, pants, hats, and sunglasses

Inactive ingredients

Isododecane, Isopropyl Palmitate, Butyloctyl Salicylate, Methyl Methacrylate Crosspolymer, Dimethicone/Bis-Isobutyl PPG-20 Crosspolymer, Caprylic/Capric Triglyceride, Polyamide-8, Isohexadecane, Polymethylsilsesquioxane, Benzotriazolyl Dodecyl p-Cresol, Dextrin Palmitate, Ethylhexyl Methoxycrylene, Polyamide-3, Pentaerythrityl Tetra-di-t-butyl Hydroxyhydrocinnamate, Tocopherol, Asiaticoside, Madecassic Acid, Asiatic Acid

Other information

- Protect the product in this container from excessive heat and direct sun

Questions?

+1-888-899-9083

Monday-Friday (9 a.m.-5 p.m. EST)

www.anua.com